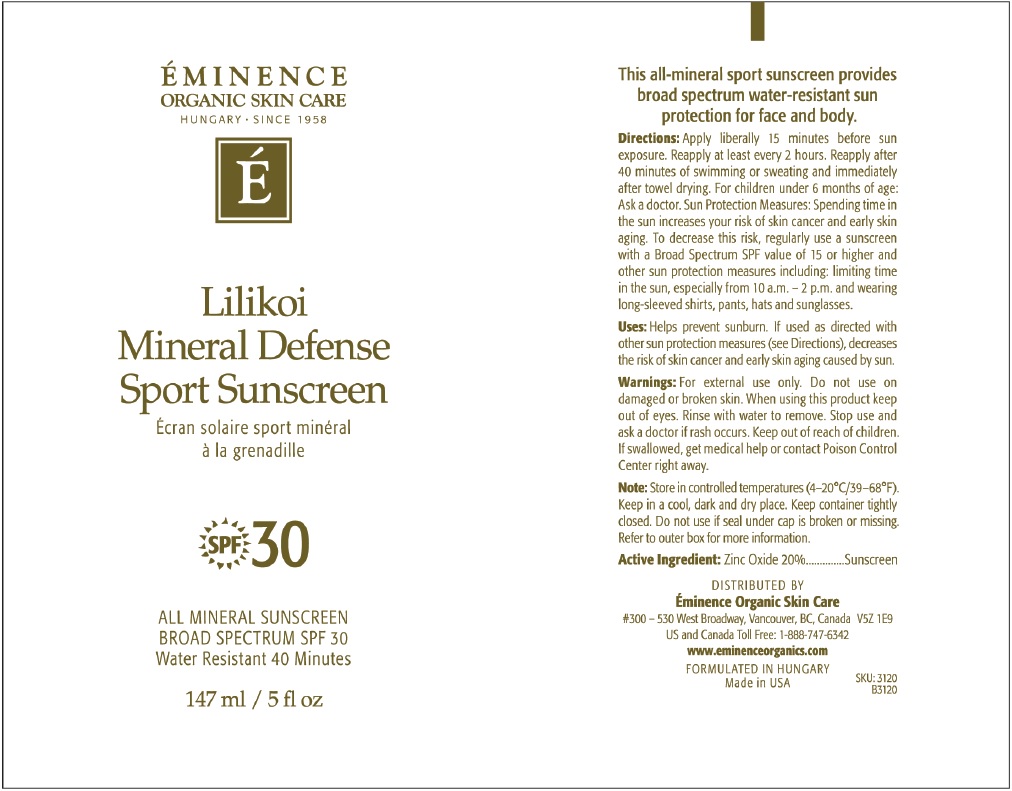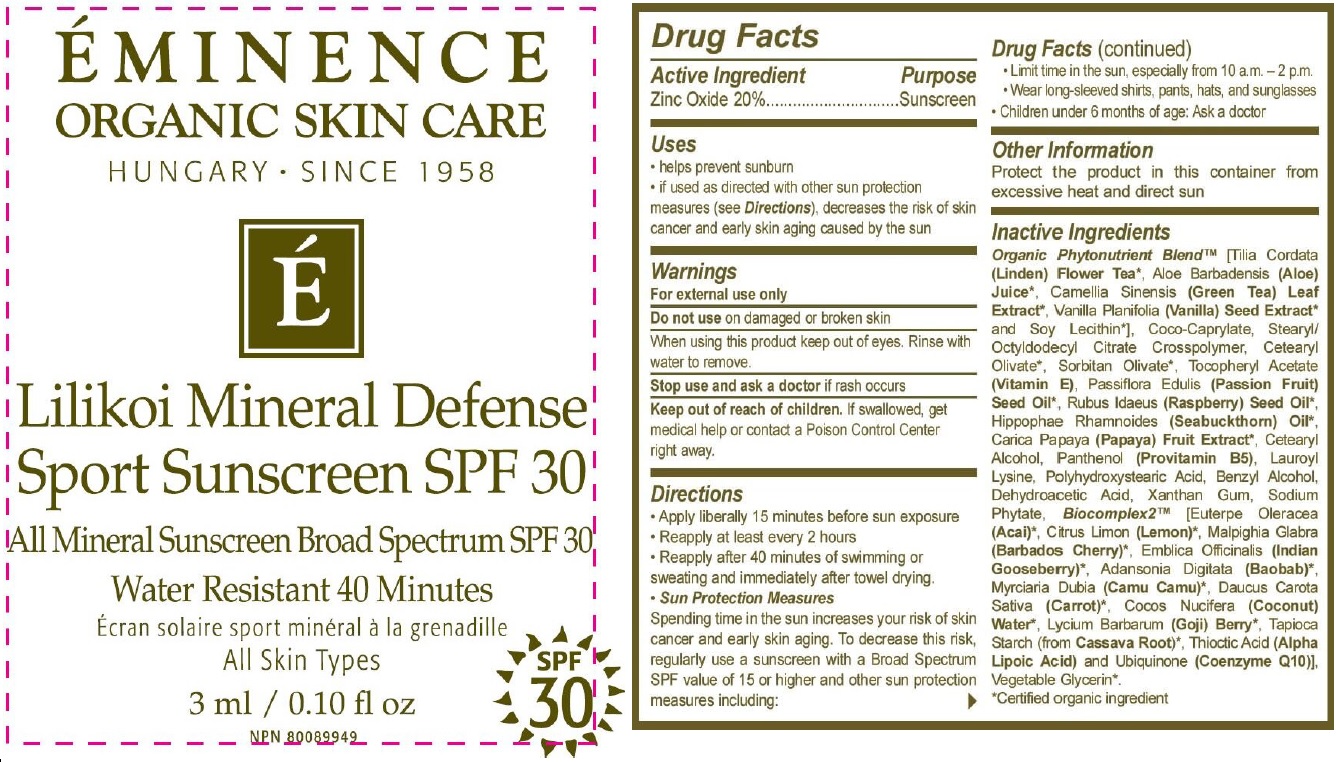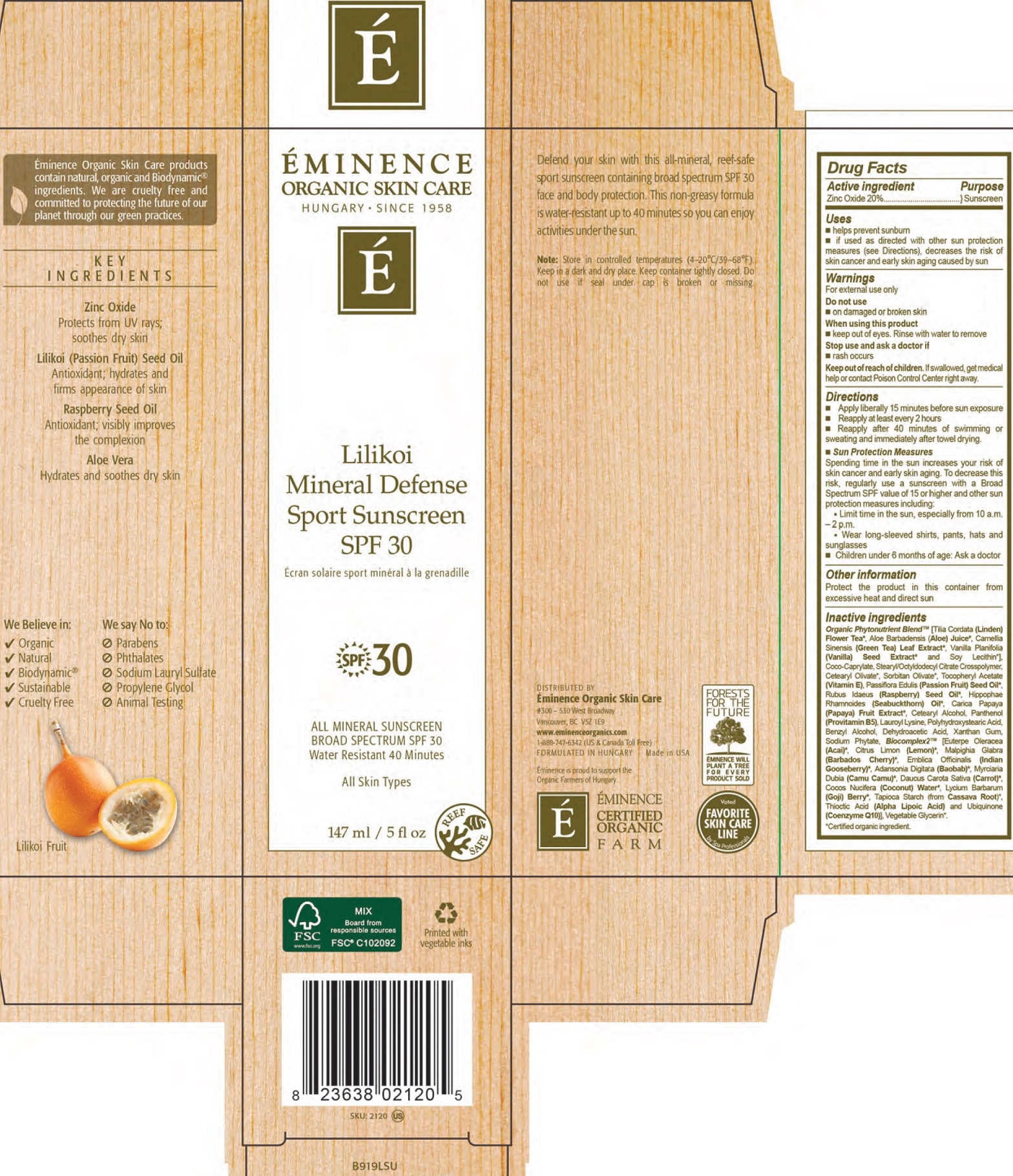 DRUG LABEL: Lilikoi Mineral Defense Sport Sunscreen SPF 30
NDC: 15751-3040 | Form: CREAM
Manufacturer: Eminence Organic Skin Care Ltd.
Category: otc | Type: HUMAN OTC DRUG LABEL
Date: 20231202

ACTIVE INGREDIENTS: ZINC OXIDE 200 mg/1 mL
INACTIVE INGREDIENTS: ALOE; GREEN TEA LEAF; VANILLA; LECITHIN, SOYBEAN; COCO-CAPRYLATE; CETEARYL OLIVATE; SORBITAN OLIVATE; PASSIFLORA EDULIS SEED OIL; RASPBERRY SEED OIL; PAPAYA; CETOSTEARYL ALCOHOL; PANTHENOL; LAUROYL LYSINE; BENZYL ALCOHOL; DEHYDROACETIC ACID; XANTHAN GUM; PHYTATE SODIUM; ACAI; LEMON; CARROT; COCONUT; WATER; THIOCTIC ACID; UBIDECARENONE

Lilikoi Mineral Defense Sport Sunscreen SPF 30

Active ingredients

Zinc Oxide 20%

Purpose

Sunscreen

Uses

- helps prevent sunburn
- if used as directed with other sun protection measures (see Directions), decreases the risk of cancer and early skin aging caused by sun

Warnings

For external use only

Do not use

- on damaged or broken skin

When using this product

- keep out of eyes. Rinse with water to remove

Stop use and ask a doctor if

- rash occurs

Keep out of reach of children.

If swallowed, get medical help or contact Poison Control Center right away.

Directions

- Apply liberally 15 minutes before sun exposure
- Reapply at least every 2 hours
- Reapply after 40 minutes of swimming or sweating and immediately after towel drying.
- Sun Protection Measures Spending time in the sun increases your risk of skin cancer and early skin aging. To decrease this risk, regularly use a sunscreen with a Broad Spectrum SPF value of 15 or higher and other sun protection measures including:
- Limit time in the sun, especially from 10 a.m. - 2 p.m.
- Wear long-sleeved shirts, pants, hats and sunglasses
- Children under 6 months of age: Ask a doctor

Other information

Protect the product in this container from excessive heat and direct sun

Inactive ingredients

Organic Phytonutrient Blend [(Tilia Cordata (Linden) Flower Tea, Aloe Barbadensis (Aloe) Juice, Camellia Sinensis (Green Tea) Leaf Extract, Vanilla Planifolia (Vanilla) Seed Extract and Soy Lecithin, Coco-Caprylate, Stearyl/Octyldodecyl Citrate Crosspolymer, Cetearyl Olivate, Sorbitan Olivate, Tocopheryl Acetate (Vitamin E), Passiflora Edulis (Passion Fruit) Seed Oil, Rubus Idaeus (Raspberry) Seed Oil, Hippohae Rhamnoides (Seabuckthorn) Oil, Carica Papaya (Papaya) Fruit Extract, Cetearyl Alcohol, Panthenol (Provitamin B5), Lauroyl Lysine, Polyhydorxystearic Acid, Benzyl Alcohol, Dehydroacetic Acid, Xanthan Gum, Sodium Phytate, Biocomplex2 (Euterpe Oleracea (Acai), Citrus Limon (Lemon), Malpighia Glabra (Barbados Cherry), Emblica Officinalis (Indian Gooseberry), Adansonia Digitata (Baobab), Myrciaria Dubia (Camu Camu), Daucus Carota Sativa (Carrot), Cocos Nucifera (Coconut), Water, Lycium Barbarum (Goji) Berry, Tapioca Starch From Cassava Root, Thioctic Acid (Alpha Lipoic Acid) and Ubiquinone (Coenzyme Q10)].
Cerified organic ingredient.